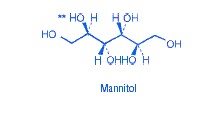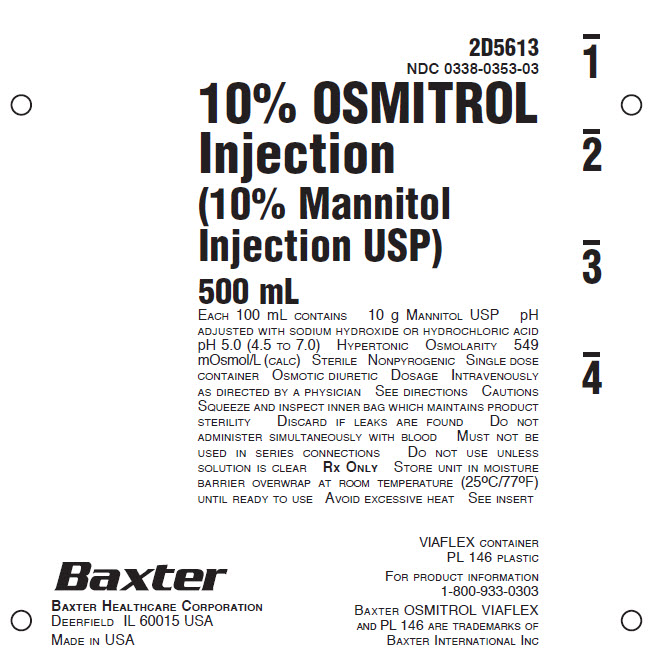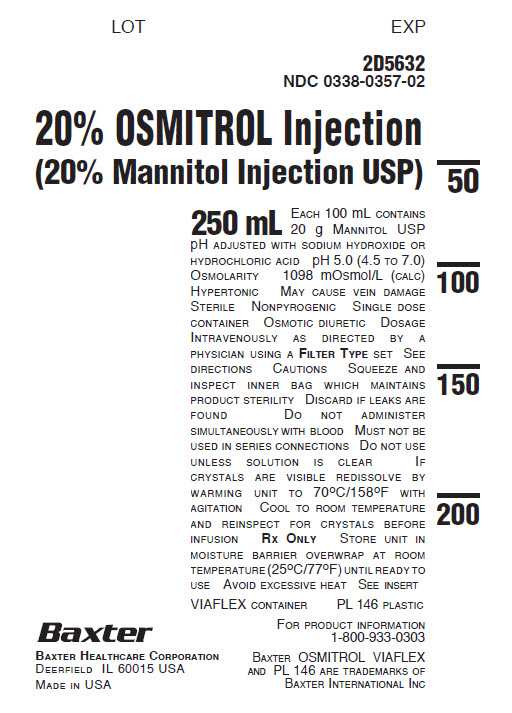 DRUG LABEL: Osmitrol
NDC: 0338-0353 | Form: INJECTION, SOLUTION
Manufacturer: Baxter Healthcare Company
Category: prescription | Type: HUMAN PRESCRIPTION DRUG LABEL
Date: 20250826

ACTIVE INGREDIENTS: MANNITOL 10 g/100 mL
INACTIVE INGREDIENTS: WATER; SODIUM HYDROXIDE; HYDROCHLORIC ACID

HIGHLIGHTS OF PRESCRIBING INFORMATION

These highlights do not include all the information needed to use OSMITROL safely and effectively. See full prescribing information for OSMITROL.
OSMITROL (mannitol injection), for intravenous use
Initial U.S. Approval: 1964

RECENT MAJOR CHANGES

Indications and Usage (removed, revised) (1) 11/2018
Contraindications (4) 11/2018
Warnings and Precautions (5.1, 5.2, 5.3, 5.4, 5.5, 5.6, 5.7) 11/2018

1 INDICATIONS AND USAGE

OSMITROL is an osmotic diuretic, indicated for the reduction of:

- intracranial pressure and treatment of cerebral edema. (1)
- elevated intraocular pressure. (1)

2 DOSAGE AND ADMINISTRATION

Administration Instructions (2.1):

- For intravenous infusion preferably into a large central vein.
- Prior to administration, evaluate renal, cardiac and pulmonary status, and correct fluid and electrolyte imbalances.

Recommended Dosage (2.2):

- The dosage, concentration and rate of administration depend on the age, weight and condition of the patient, including fluid requirement, urinary output and concomitant therapy.
- Reduction of Intracranial Pressure: 0.25 gram/kg administered every 6 to 8 hours as an intravenous infusion over 30 minutes.
- Reduction of Intraocular Pressure: 1.5 to 2 grams/kg of a 15% or 20% w/v solution as a single dose administered intravenously over at least 30 minutes.

3 DOSAGE FORMS AND STRENGTHS

Injection (3):

- 10% (0.1 grams/mL): 10 grams of mannitol, USP per 100 mL in a single-dose 500 mL flexible container
- 20% (0.2 grams/mL): 20 grams of mannitol, USP per 100 mL in single-dose 250 mL and 500 mL flexible containers

4 CONTRAINDICATIONS

- Known hypersensitivity to mannitol. (4, 5.1)
- Anuria. (4, 5.2)
- Severe hypovolemia. (4, 5.4)
- Pre-existing severe pulmonary vascular congestion or pulmonary edema. (4, 5.5)
- Active intracranial bleeding except during craniotomy. (4)

5 WARNINGS AND PRECAUTIONS

- Hypersensitivity Reactions, including anaphylaxis: Stop infusion immediately if hypersensitivity reactions develop. (5.1)
- Renal Complications Including Renal Failure: Risk factors include pre-existing renal failure, concomitant use of nephrotoxic drugs or other diuretics. Avoid use of nephrotoxic drugs. Discontinue OSMITROL if renal function worsens. (5.2, 8.6)
- Central Nervous System (CNS) Toxicity: Confusion, lethargy and coma may occur during or after infusion. Concomitant neurotoxic drugs may potentiate toxicity. Avoid use of neurotoxic drugs. Discontinue OSMITROL if CNS toxicity develops. (5.3)
- Fluid and Electrolyte Imbalances, Hyperosmolarity: Hypervolemia may exacerbate congestive heart failure, hyponatremia can lead to encephalopathy; hypo/hyperkalemia can result in cardiac adverse reactions in sensitive patients. Discontinue OSMITROL if fluid and/or electrolyte imbalances occur. (5.4)
- Monitoring/Laboratory Tests: Monitor fluid and electrolytes, serum osmolarity and renal, cardiac and pulmonary function. Discontinue if toxicity develops. (5.5)
- Infusion Site Reactions: May include irritation and inflammation, as well as severe reactions (compartment syndrome) when associated with extravasation. (5.6)
- Interference with Laboratory Tests: High concentrations of mannitol may cause false low results of inorganic phosphorus blood concentrations. Mannitol may produce false positive results for blood ethylene glycol. (5.7, 7.6)

6 ADVERSE REACTIONS

The most common adverse reactions are hypersensitivity reactions, renal failure, CNS toxicity, hypo/hypervolemia, hypo/hypernatremia, hypo/hyperkalemia, and infusion site reactions. (6)

To report SUSPECTED ADVERSE REACTIONS, contact Baxter Healthcare at 1-866-888-2472 or FDA at 1-800-FDA-1088 or www.fda.gov/medwatch.

7 DRUG INTERACTIONS

- Nephrotoxic Drugs and Diuretics: May increase the risk of renal failure; avoid concomitant use. (7.1, 7.2)
- Neurotoxic Drugs: May potentiate CNS toxicity of mannitol; avoid concomitant use. (7.3)
- Drugs Affected by Electrolyte Imbalances: May result in cardiac adverse reactions; monitor serum electrolytes and discontinue OSMITROL if cardiac status worsens. (7.4)
- Renally Eliminated Agents: Concomitant use may decrease the effectiveness of agents that undergo significant renal elimination. However, concomitant use of mannitol and lithium may increase risk of lithium toxicity. If concomitant use is necessary, frequently monitor lithium concentrations and for signs of toxicity. (7.5)

FULL PRESCRIBING INFORMATION

1 INDICATIONS AND USAGE

OSMITROL is indicated for:

- The reduction of intracranial pressure and treatment of cerebral edema;
- The reduction of elevated intraocular pressure.

2 DOSAGE AND ADMINISTRATION

2.1 Important Preparation and Administration Instructions

- OSMITROL is for intravenous infusion preferably into a large central vein [see Warnings and Precautions (5.5), Description (11)].
- Prior to administration of OSMITROL, evaluate renal, cardiac and pulmonary status of the patient and correct fluid and electrolyte imbalances [see Dosage and Administration (2.2)].
- Do not administer OSMITROL simultaneously with blood products through the same administration set because of the possibility of pseudoagglutination or hemolysis.

Preparation

1. Tear overwrap down side at slit and remove solution container.
2. Visually inspect the container. Do not administer unless solution is clear and seal is intact.
  1. If the outlet port protector is damaged, detached, or not present, discard container as solution path sterility may be impaired.
  2. Some opacity of the plastic due to moisture absorption during the sterilization process may be observed. This is normal and does not affect the solution quality or safety. The opacity will diminish gradually.
3. Check for minute leaks by squeezing inner bag firmly. If leaks are found, discard solution as sterility may be impaired.
4. Admixing OSMITROL with other medications is not recommended.
5. Inspect OSMITROL visually for particulate matter and discoloration prior to administration. If particulates or discoloration are present, discard the bag.
6. OSMITROL solutions may crystallize when exposed to low temperature. At higher concentrations, the solutions have a greater tendency to crystallize. Inspect OSMITROL for crystals prior to administration. If crystals are visible, re-dissolve by warming the solution up to 70°C, with agitation. Solutions should not be heated in water or in a microwave oven due to potential for product contamination or damage. Allow the solution to cool to room or body temperature before re-inspection for crystals and use.

Administration

1. Suspend container from eyelet support.
2. Remove protector from outlet port at bottom of container.
3. Attach administration set. Refer to complete directions accompanying set.
4. Use administration sets with a final in-line filter because of the potential for OSMITROL crystals to form.
5. To prevent air embolism, use a non-vented infusion set or close the vent on a vented set, avoid multiple connections, do not connect flexible containers in series, fully evacuate residual gas in the container prior to administration, do not pressurize the flexible container to increase flow rates, and if administration is controlled by a pumping device, turn off pump before the container runs dry.
6. For single use only; discard unused portion.

2.2 Recommended Dosage

Prior to administration of OSMITROL, evaluate renal, cardiac and pulmonary status of the patient and correct fluid and electrolyte imbalances.

The total dosage, concentration, and rate of administration depend on the age, weight, and condition of the patient being treated, including fluid requirement, electrolyte balance, serum osmolality, urinary output, and concomitant therapy.

The following outline of administration and dosage is only a general guide to therapy.

Reduction of Intracranial Pressure
Usually a maximum reduction in intracranial pressure can be achieved with a dose of 0.25 gram/kg given intravenously as an intravenous infusion over 30 minutes which may be repeated every six to eight hours.

During and following OSMITROL infusion, monitor fluid and electrolytes, serum osmolarity, and renal, cardiac and pulmonary function. Discontinue OSMITROL if renal, cardiac, or pulmonary status worsens or CNS toxicity develops [see Warnings and Precautions (5.2, 5.3, 5.4, 5.5)].

Reduction of Intraocular Pressure

The recommended dosage is 1.5 to 2 grams/kg of a 20% w/v solution (7.5 to 10 mL/kg) or as a 15% w/v solution (10 to 13 mL/kg) as a single dose administered intravenously over at least 30 minutes. When used preoperatively, administer OSMITROL sixty to ninety minutes before surgery to achieve maximal reduction of intraocular pressure before operation.

3 DOSAGE FORMS AND STRENGTHS

OSMITROL Injection:

- 10% (0.1 grams/mL): 10 grams of mannitol, USP per 100 mL in a single-dose 500 mL flexible container
- 20% (0.2 grams/mL): 20 grams of mannitol, USP per 100 mL in single-dose 250 mL and 500 mL flexible containers

4 CONTRAINDICATIONS

OSMITROL is contraindicated in patients with:

- Known hypersensitivity to mannitol [see Warnings and Precautions (5.1)]
- Anuria [see Warnings and Precautions (5.2)]
- Severe hypovolemia [see Warnings and Precautions (5.4)]
- Pre-existing severe pulmonary vascular congestion or pulmonary edema [see Warnings and Precautions (5.5)]
- Active intracranial bleeding except during craniotomy

5 WARNINGS AND PRECAUTIONS

5.1 Hypersensitivity Reactions

Serious hypersensitivity reactions, including anaphylaxis, hypotension and dyspnea resulting in cardiac arrest and death have been reported with OSMITROL [see Adverse Reactions (6)].

Stop the infusion immediately if signs or symptoms of a suspected hypersensitivity reaction develop. Initiate appropriate therapeutic countermeasures as clinically indicated.

5.2 Renal Complications Including Renal Failure

Renal complications, including irreversible renal failure have been reported in patients receiving mannitol. Reversible, oliguric acute kidney injury (AKI) has occurred in patients with normal pretreatment renal function who received large intravenous doses of mannitol. Although the osmotic nephrosis associated with mannitol administration is in principle reversible, osmotic nephrosis in general is known to potentially proceed chronic or even end-stage renal failure. Monitor renal function closely, including signs of urine output reduction, during OSMITROL infusion. Patients with pre-existing renal disease, patients with conditions that put them at high risk for renal failure, or those receiving potentially nephrotoxic drugs or other diuretics, are at increased risk of renal failure following administration of OSMITROL. Avoid concomitant administration of nephrotoxic drugs (e.g., aminoglycosides) or, other diuretics with OSMITROL, if possible [see Drug Interactions (7.1, 7.2)].

Patients with oliguric AKI who subsequently develop anuria while receiving mannitol are at risk of congestive heart failure, pulmonary edema, hypertensive crisis, coma and death.

During and following OSMITROL infusion for the reduction in intracranial pressure, monitor the patient clinically and laboratory tests for changes in fluid and electrolyte status. Discontinue OSMITROL if renal function worsens. [see Warnings and Precautions (5.5)].

5.3 Central Nervous System (CNS) Toxicity

CNS toxicity manifested by, e.g., confusion, lethargy, coma has been reported in patients treated with mannitol, some resulting in death, in particular in the presence of impaired renal function CNS toxicity may result from high serum mannitol concentrations, serum hyperosmolarity resulting in intracellular dehydration within CNS, hyponatremia or other disturbances of electrolyte and acid/base balance secondary to mannitol administration [see Warnings and Precautions (5.4)].

At high concentrations, mannitol may cross the blood brain barrier and interfere with the ability of the brain to maintain the pH of the cerebrospinal fluid especially in the presence of acidosis.

In patients with preexisting compromise of the blood brain barrier, the risk of increasing cerebral edema (general and focal) associated with repeated or continued use of OSMITROL must be individually weighed against the expected benefits.

A rebound increase of intracranial pressure may occur several hours after the infusion. Patients with a compromised blood brain barrier are at increased risk.

Concomitant administration of neurotoxic drugs (e.g., aminoglycosides) with OSMITROL may potentiate neurotoxicity. Avoid concomitant use of neurotoxic drugs, if possible [see Drug Interactions (7.3)].

During and following OSMITROL infusion for the reduction in intracranial pressure, monitor the patient clinically and laboratory tests for changes in fluid and electrolyte status. Discontinue OSMITROL if CNS toxicity develops [see Warnings and Precautions (5.5)].

5.4 Fluid and Electrolyte Imbalances, Hyperosmolarity

Depending on dosage and duration, administration of OSMITROL may result in hypervolemia leading to or exacerbating existing congestive heart failure. Accumulation of mannitol due to insufficient renal excretion increases the risk of hypervolemia. Mannitol-induced osmotic diuresis may cause or worsen dehydration/hypovolemia and hemoconcentration. Administration of OSMITROL may also cause hyperosmolarity [see Description (11)].

Depending on dosage and duration of administration, electrolyte and acid/base imbalances may also result from transcellular shifts in water and electrolytes, osmotic diuresis and/or other mechanisms. Such imbalances may be severe and potentially fatal.

Imbalances that may result from OSMITROL administration include:

- Hypernatremia, dehydration and hemoconcentration
- Hyponatremia, which can lead to headache, nausea, seizures, lethargy, coma, cerebral edema, and death. Acute symptomatic hyponatremic encephalopathy is considered a medical emergency.
- Hypo/hyperkalemia. The development of electrolyte imbalances (e.g., hyperkalemia, hypokalemia) associated with mannitol administration may result in cardiac adverse reactions in patients receiving drugs that are sensitive to such imbalances (e.g., digoxin, agents that may cause QT prolongation, neuromuscular blocking agents) [see Drug Interactions (7.4)].
- Other electrolyte disturbances
- Metabolic acidosis/alkalosis

Pediatric patients less than two years of age, particularly preterm and term neonates, may be at higher risk for fluid and electrolyte abnormalities following OSMITROL administration due to decreased glomerular filtration rate and limited ability to concentrate urine [see Use in Specific Populations (8.4)].

During and following OSMITROL infusion for the reduction in intracranial pressure, monitor fluid and electrolyte status and discontinue OSMITROL if imbalances occur [see Warnings and Precautions (5.5)].

5.5 Monitoring/Laboratory Tests

During and following OSMITROL infusion for the reduction in intracranial pressure, monitor:

- serum osmolarity, serum electrolytes (including sodium, potassium, calcium and phosphate) and acid base balance,
- the osmol gap
- signs of hypo- or hypervolemia, including urine output
- renal, cardiac and pulmonary function
- intracranial pressure

Discontinue OSMITROL if renal, cardiac, or pulmonary status worsens or CNS toxicity develops [see Contraindications (4)].

5.6 Infusion Site Reactions

The infusion of hypertonic solutions through a peripheral vein, including OSMITROL at a concentration of 10% w/v or greater, may result in peripheral venous irritation, including phlebitis. Other severe infusion site reactions, such as compartment syndrome and swelling associated with extravasation, can occur with administration of OSMITROL [see Adverse Reactions (6)]. OSMITROL is preferably for administration into a large central vein [see Dosage and Administration (2.1)].

5.7 Interference with Laboratory Tests

High concentrations of mannitol can cause false low results for inorganic phosphorus blood concentrations [see Drug Interactions (7.6)].

Mannitol may produce false positive results in tests for blood ethylene glycol concentrations [see Drug Interactions (7.6)].

6 ADVERSE REACTIONS

The following adverse reactions from voluntary reports or clinical studies have been reported with OSMITROL. Because many of these reactions were reported voluntarily from a population of uncertain size, it is not always possible to reliably estimate their frequency or establish a causal relationship to drug exposure.

- Hypersensitivity reactions: cardiac arrest, anaphylaxis, hypotension, dyspnea, hypertension, pyrexia, chills, sweating, cough, musculoskeletal stiffness, myalgia, urticarial/rash, pruritus, generalized pain, discomfort, nausea, vomiting, and headache. [see Warnings and Precautions (5.1)]
- Renal Failure: acute kidney injury, osmotic nephrosis, azotemia, anuria, hematuria, oliguria, polyuria [see Warnings and Precautions (5.2)]
- CNS Toxicity: coma, seizures, confusion, lethargy; rebound increase in intracranial pressure; dizziness [see Warnings and Precautions (5.3)]
- Fluid and Electrolyte Imbalances: hypovolemia, hypervolemia, peripheral edema, dehydration, hyponatremia, hypernatremia, hyperkalemia, hypokalemia; metabolic acidosis [see Warnings and Precautions (5.4)]
- Infusion Site Reactions: phlebitis, inflammation, pain, rash, erythema, pruritus; compartment syndrome and swelling associated with extravasation [see Warnings and Precautions (5.6)]
- Cardiac and Respiratory Disorders: congestive cardiac failure, pulmonary edema, palpitations
- Gastrointestinal Disorders: thirst, dry mouth
- General Disorders: asthenia, malaise

7 DRUG INTERACTIONS

7.1 Nephrotoxic Drugs

Concomitant administration of nephrotoxic drugs (e.g., cyclosporine, aminoglycosides) increases the risk of renal failure following administration of mannitol. Avoid use of nephrotoxic drugs with OSMITROL, if possible [see Warnings and Precautions (5.2)].

7.2 Diuretics

Concomitant administration of other diuretics may potentiate the renal toxicity of mannitol. Avoid use of other diuretics with OSMITROL, if possible [see Warnings and Precautions (5.2)].

7.3 Neurotoxic Drugs

Concomitant administration of systemic neurotoxic drugs (e.g., aminoglycosides) with OSMITROL may potentiate the CNS toxicity of mannitol. Avoid use of systemic neurotoxic drugs with OSMITROL, if possible [see Warnings and Precautions (5.3)].

7.4 Drugs Affected by Electrolyte Imbalances

The development of electrolyte imbalances (e.g., hyperkalemia, hypokalemia) associated with mannitol administration may result in cardiac adverse reactions in patients receiving drugs that are sensitive to such imbalances (e.g., digoxin, drugs that prolong the QT interval, neuromuscular blocking agents) [see Warnings and Precautions (5.4)]. During and following OSMITROL infusion, monitor serum electrolytes and discontinue OSMITROL if cardiac status worsens [see Warnings and Precautions (5.5)].

7.5 Renally Eliminated Drugs

Mannitol therapy may increase the elimination, and decrease the effectiveness of treatment with, drugs that undergo significant renal elimination. Concomitant administration of mannitol with lithium may initially increase the elimination of lithium but may also increase the risk of lithium toxicity if patients develop hypovolemia or renal impairment. In patients receiving lithium, consider holding lithium doses during treatment with OSMITROL. In patients requiring concomitant administration of lithium and OSMITROL, frequently monitor serum lithium concentrations and for signs of lithium toxicity.

7.6 Interference with Laboratory Tests

High concentrations of mannitol can cause false low results for inorganic phosphorus blood concentrations when an assay based on the conversion of phosphate (orthophosphate) to the phosphomolybdate complex is used.

Mannitol may produce false positive results in tests for blood ethylene glycol concentrations in which mannitol is initially oxidized to an aldehyde.

8 USE IN SPECIFIC POPULATIONS

8.1 Pregnancy

Risk Summary

The available case report data with mannitol over decades of use have not identified a drug-associated risk of major birth defects, miscarriage or adverse maternal or fetal outcomes. Mannitol crosses the placenta and may cause fluid shifts that could potentially result in adverse effects in the fetus (see Data). No adverse developmental effects from mannitol were reported in published animal studies; however, fluid shifts occurred in fetal ewes in response to maternal infusion of mannitol.

The estimated background risk of major birth defects and miscarriage for the indicated population is unknown. All pregnancies have a background risk of birth defect, loss, or other adverse outcomes. In the U.S. general population, the estimated background risk of major birth defects and miscarriage in clinically recognized pregnancies is 2 to 4% and 15 to 20%, respectively.

Data

Human Data

Published literature reports the presence of mannitol in amniotic fluid when mannitol is administered to pregnant women during the third trimester of pregnancy.

8.2 Lactation

Risk Summary

There are no data on the presence of mannitol in either human or animal milk, the effects on the breastfed infant, or the effects on milk production. The developmental and health benefits of breastfeeding should be considered along with the mother’s clinical need for OSMITROL and any potential adverse effects on the breastfed infant from OSMITROL or from the underlying maternal condition.

8.4 Pediatric Use

OSMITROL is approved for use in the pediatric population for the reduction of intracranial and intraocular pressure. Studies have not defined the optimal dose of OSMITROL in the pediatric population. The safety profile for mannitol use in pediatric patients is similar to adults at dosages described in labeling. However, pediatric patients less than two years of age, particularly preterm and term neonates, may be at higher risk for fluid and electrolyte abnormalities following OSMITROL administration due to decreased glomerular filtration rate and limited ability to concentrate urine [see Warnings and Precautions (5.4)].

8.5 Geriatric Use

Mannitol is known to be substantially excreted by the kidney and the risk of adverse reactions to this drug may be greater in elderly patients with impaired renal function. Evaluate the renal, cardiac and pulmonary status of the patient and correct fluid and electrolyte imbalances prior to administration of OSMITROL [see Warnings and Precautions (5.2, 5.3, 5.4, 5.5)].

8.6 Renal Impairment

Patients with pre-existing renal disease, patients with conditions that put them at high risk for renal failure, or those receiving potentially nephrotoxic drugs or other diuretics, are at increased risk of renal failure with administration of mannitol. Evaluate the renal, cardiac and pulmonary status of the patient and correct fluid and electrolyte imbalances prior to administration of OSMITROL [see Warnings and Precautions (5.2, 5.3, 5.4, 5.5)].

10 OVERDOSAGE

Signs and symptoms of overdose with OSMITROL include renal failure and AKI, hypo/hypervolemia, hyperosmolarity and electrolyte imbalances, CNS toxicity (e.g., coma, seizures), some of which can be fatal [see Warnings and Precautions (5.2, 5.3, 5.4)].

Management of overdosage with OSMITROL is symptomatic and supportive. Discontinue the infusion and institute appropriate corrective measures with particular attention to renal, cardiac and pulmonary systems. Correct fluid and electrolyte imbalances.

OSMITROL is dialyzable (hemodialysis and peritoneal dialysis), hemodialysis may increase OSMITROL elimination.

11 DESCRIPTION

OSMITROL is a sterile, nonpyrogenic solution of Mannitol, USP in a single-dose flexible container for intravenous administration as an osmotic diuretic. It contains no antimicrobial agents. Mannitol is a six carbon sugar alcohol prepared commercially by the reduction of dextrose. The pH is adjusted with sodium hydroxide or hydrochloric acid. Composition, osmolarity, and pH are shown in Table 1.

Table 1 | Size | Composition | [Normal physiologic osmolarity range is approximately 280 to 310 mOsmol/L.] Osmolarity | pH
Table 1 | (mL) | Mannitol, USP (g/L) | (mOsmol/L) (calc)
10% OSMITROL | 500 | 100 | 549 | 5.0 (4.5 TO 7.0)
20% OSMITROL | 250 | 200 | 1098 | 5.0 (4.5 TO 7.0)
20% OSMITROL | 500 | 200 | 1098 | 5.0 (4.5 TO 7.0)

The plastic container is fabricated from a specially formulated polyvinyl chloride (PL 146 Plastic). The amount of water that can permeate from inside the container into the overwrap is insufficient to affect the solution significantly. Solutions in contact with the plastic container can leach out certain of its chemical components in very small amounts within the expiration period, e.g., di-2-ethylhexyl phthalate (DEHP), up to 5 parts per million. However, the safety of the plastic has been confirmed in tests in animals according to USP biological tests for plastic containers as well as by tissue culture toxicity studies.

12 CLINICAL PHARMACOLOGY

12.1 Mechanism of Action

Mannitol, when administered intravenously, exerts its osmotic diuretic effect as a solute of relatively small molecular size being largely confined to the extracellular space. Mannitol hinders tubular reabsorption of water and enhances excretion of sodium and chloride by elevating the osmolarity of the glomerular filtrate.

This increase in extracellular osmolarity affected by the intravenous administration of mannitol will induce the movement of intracellular water to the extracellular and vascular spaces. This action underlies the role of mannitol in reducing intracranial pressure, intracranial edema, and intraocular pressure.

12.3 Pharmacokinetics

Distribution

Mannitol distributes largely in the extracellular space in 20 to 40 minutes after intravenous administration. The volume of distribution of mannitol is approximately 17 L in adults.

Elimination

In subjects with normal renal function, the total clearance is 87 to 109 mL/min. The elimination half-life of mannitol is 0.5 to 2.5 hours.

Metabolism

Only relatively small amount of the dose administered is metabolized after intravenous administration of mannitol to healthy subjects.

Excretion

Mannitol is eliminated primarily via the kidneys in unchanged form. Mannitol is filtered by the glomeruli, exhibits less than 10% of tubular reabsorption, and is not secreted by tubular cells. Following intravenous administration, approximately 80% of an administered dose of mannitol is estimated to be excreted in the urine in three hours with lesser amounts thereafter.

Specific Populations

Patients with Renal Impairment

In patients with renal impairment, the elimination half-life of mannitol is prolonged. In a published study, in patients with renal impairment including acute renal failure and end stage renal failure, the elimination half-life of mannitol was estimated at about 36 hours, based on serum osmolarity. In patients with renal impairment on dialysis, the elimination half-life of mannitol was reduced to 6 and 21 hours during hemodialysis and peritoneal dialysis, respectively. [see Use in Specific Populations (8.6), Overdosage (10)].

16 HOW SUPPLIED/STORAGE AND HANDLING

OSMITROL injection is supplied in single-dose, flexible VIAFLEX plastic containers and is available as follows:

Code | Size (mL) | NDC | Product Name
2D5613 | 500 | 0338-0353-03 | 10% (0.1 g/mL mannitol, USP)
2D5632 | 250 | 0338-0357-02 | 20% (0.2 g/mL mannitol, USP)
2D5633 | 500 | 0338-0357-03 | 20% (0.2 g/mL mannitol, USP)

Do not remove container from overwrap until intended for use.

Exposure of pharmaceutical products to heat should be minimized. Avoid excessive heat. Store at room temperature (25°C); brief exposure up to 40°C does not adversely affect the product.

17 PATIENT COUNSELING INFORMATION

Inform patients or caregivers of the following risks of OSMITROL:

- Hypersensitivity Reactions [see Warnings and Precautions (5.1)]
- Renal Failure [see Warnings and Precautions (5.2)]
- CNS Toxicity [see Warnings and Precautions (5.3)]
- Fluid and Electrolyte Imbalances, Hyperosmolarity [see Warnings and Precautions (5.4)]
- Infusion Site Reactions [see Warnings and Precautions (5.6)]

Manufactured by:
Baxter Healthcare Corporation
Deerfield, IL 60015 USA

Printed in USA

Baxter, Osmitrol, and Viaflex are trademarks of Baxter International Inc.

07-19-00-9763

PACKAGE/LABEL PRINCIPAL DISPLAY PANEL

Container Label

2D5613
NDC 0338-0353-03

10% OSMITROL
Injection
(10% Mannitol
Injection USP)

500 mL

EACH 100 mL CONTAINS 10 g MANNITOL USP pH
ADJUSTED WITH SODIUM HYDROXIDE OR HYDROCHLORIC ACID
pH 5.0 (4.5 TO 7.0) HYPERTONIC OSMOLARITY 549
mOsmol/L (CALC) STERILE NONPYROGENIC SINGLE DOSE
CONTAINER OSMOTIC DIURETIC DOSAGE INTRAVENOUSLY
AS DIRECTED BY A PHYSICIAN SEE DIRECTIONS CAUTIONS
SQUEEZE AND INSPECT INNER BAG WHICH MAINTAINS PRODUCT
STERILITY DISCARD IF LEAKS ARE FOUND DO NOT
ADMINISTER SIMULTANEOUSLY WITH BLOOD MUST NOT BE
USED IN SERIES CONNECTIONS DO NOT USE UNLESS
SOLUTION IS CLEAR RX ONLY STORE UNIT IN MOISTURE
BARRIER OVERWRAP AT ROOM TEMPERATURE (25°C/77ºF)
UNTIL READY TO USE AVOID EXCESSIVE HEAT SEE INSERT

VIAFLEX CONTAINER
PL 146 PLASTIC

FOR PRODUCT INFORMATION
1-800-933-0303

BAXTER OSMITROL VIAFLEX
AND PL 146 ARE TRADEMARKS OF
BAXTER INTERNATIONAL INC

BAXTER HEALTHCARE CORPORATION
DEERFIELD IL 60015 USA
MADE IN USA

Container Label

LOT EXP

2D5632
NDC 0338-0357-02

20% OSMITROL Injection
(20% Mannitol Injection USP)

250 mL EACH 100 mL CONTAINS
20 g MANNITOL USP
pH ADJUSTED WITH SODIUM HYDROXIDE OR
HYDROCHLORIC ACID pH 5.0 (4.5 TO 7.0)
OSMOLARITY 1098 mOsmol/L (CALC)
HYPERTONIC MAY CAUSE VEIN DAMAGE
STERILE NONPYROGENIC SINGLE DOSE
CONTAINER OSMOTIC DIURETIC DOSAGE
INTRAVENOUSLY AS DIRECTED BY A
PHYSICIAN USING A FILTER TYPE SET SEE
DIRECTIONS CAUTIONS SQUEEZE AND
INSPECT INNER BAG WHICH MAINTAINS
PRODUCT STERILITY DISCARD IF LEAKS ARE
FOUND DO NOT ADMINISTER
SIMULTANEOUSLY WITH BLOOD MUST NOT BE
USED IN SERIES CONNECTIONS DO NOT USE
UNLESS SOLUTION IS CLEAR IF
CRYSTALS ARE VISIBLE REDISSOLVE BY
WARMING UNIT TO 70°C/158°F WITH
AGITATION COOL TO ROOM TEMPERATURE
AND REINSPECT FOR CRYSTALS BEFORE
INFUSION RX ONLY STORE UNIT IN
MOISTURE BARRIER OVERWRAP AT ROOM
TEMPERATURE (25°C/77ºF) UNTIL READY TO
USE AVOID EXCESSIVE HEAT SEE INSERT

VIAFLEX CONTAINER PL 146 PLASTIC

FOR PRODUCT INFORMATION
1-800-933-0303

BAXTER OSMITROL VIAFLEX
AND PL 146 ARE TRADEMARKS OF
BAXTER INTERNATIONAL INC

BAXTER HEALTHCARE CORPORATION
DEERFIELD IL 60015 USA
MADE IN USA